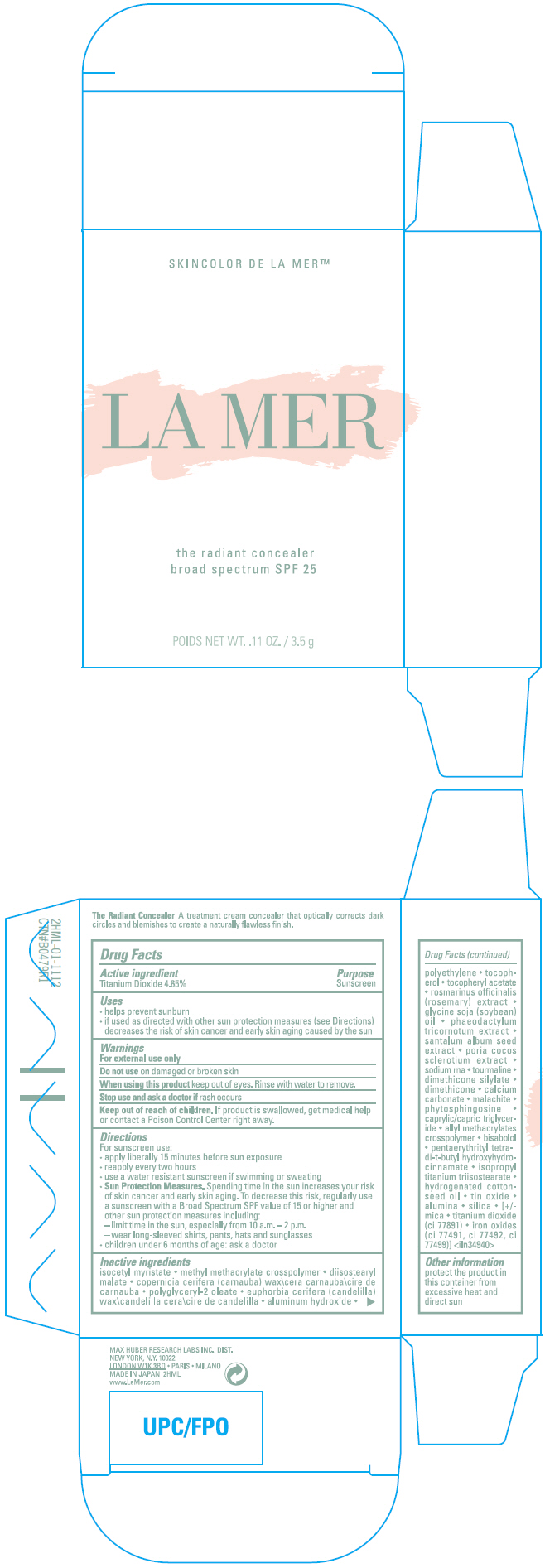 DRUG LABEL: THE RADIANT CONCEALER BROAD SPECTRUM SPF 25
NDC: 65966-015 | Form: CREAM
Manufacturer: MAX HUBER RESEARCH LAB INC
Category: otc | Type: HUMAN OTC DRUG LABEL
Date: 20150504

ACTIVE INGREDIENTS: Titanium Dioxide 3.5 g/100 g
INACTIVE INGREDIENTS: isocetyl myristate; diisostearyl malate; carnauba wax; candelilla wax; aluminum hydroxide; high density polyethylene; tocopherol; .alpha.-tocopherol acetate; rosemary; soybean oil; phaeodactylum tricornutum; santalum album seed; dimethicone; calcium carbonate; phytosphingosine; medium-chain triglycerides; levomenol; pentaerythritol tetrakis(3-(3,5-di-tert-butyl-4-hydroxyphenyl)propionate); isopropyl titanium triisostearate; hydrogenated cottonseed oil; stannic oxide; aluminum oxide; silicon dioxide; mica; ferric oxide red; ferric oxide yellow; ferrosoferric oxide

THE RADIANT CONCEALER BROAD SPECTRUM SPF 25

Drug Facts

Active ingredient

Titanium Dioxide 4.65%

Purpose

Sunscreen

Uses

- helps prevent sunburn
- if used as directed with other sun protection measures (see Directions) decreases the risk of skin cancer and early skin aging caused by the sun

Warnings

For external use only

Do not use on damaged or broken skin

When using this product keep out of eyes. Rinse with water to remove.

Stop use and ask a doctor if rash occurs

Keep out of reach of children. If product is swallowed, get medical help or contact a Poison Control Center right away.

Directions

For sunscreen use:

- apply liberally 15 minutes before sun exposure
- reapply every two hours
- use a water resistant sunscreen if swimming or sweating
- Sun Protection Measures. Spending time in the sun increases your risk of skin cancer and early skin aging. To decrease this risk, regularly use a sunscreen with a Broad Spectrum SPF value of 15 or higher and other sun protection measures including:
  - limit time in the sun, especially from 10 a.m. – 2 p.m.
  - wear long-sleeved shirts, pants, hats and sunglasses
- children under 6 months of age: ask a doctor

Inactive ingredients

isocetyl myristate • methyl methacrylate crosspolymer • diisostearyl malate • copernicia cerifera (carnauba) wax\cera carnauba\cire de carnauba • polyglyceryl-2 oleate • euphorbia cerifera (candelilla) wax\candelilla cera\cire de candelilla • aluminum hydroxide • polyethylene • tocopherol • tocopheryl acetate • rosmarinus officinalis (rosemary) extract • glycine soja (soybean) oil • phaeodactylum tricornotum extract • santalum album seed extract • poria cocos sclerotium extract • sodium rna • tourmaline • dimethicone silylate • dimethicone • calcium carbonate • malachite • phytosphingosine • caprylic/capric triglyceride • allyl methacrylates crosspolymer • bisabolol • pentaerythrityl tetra-di-t-butyl hydroxyhydrocinnamate • isopropyl titanium triisostearate • hydrogenated cottonseed oil • tin oxide • alumina • silica • [+/-mica • titanium dioxide (ci 77891) • iron oxides (ci 77491, ci 77492, ci 77499)] <iln34940>

Other information

protect the product in this container from excessive heat and direct sun

PRINCIPAL DISPLAY PANEL - 3.5 g Container Carton

SKINCOLOR DE LA MER™

LA MER

the radiant concealer
broad spectrum SPF 25

POIDS NET WT. .11 OZ. / 3.5 g